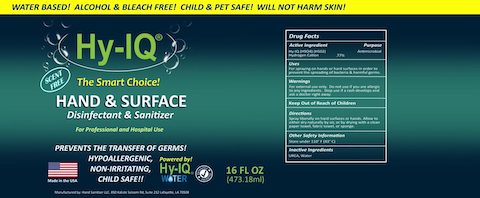 DRUG LABEL: Hy-IQ Hand and Surface Disinfectant and Sanitizer
NDC: 76701-362 | Form: SPRAY
Manufacturer: HAND SANITIZER LLC
Category: otc | Type: HUMAN OTC DRUG LABEL
Date: 20210715

ACTIVE INGREDIENTS: HYDROGEN CATION 10 mg/1 mL
INACTIVE INGREDIENTS: WATER 940 mg/1 mL; UREA 50 mg/1 mL

ACTIVE INGREDIENT

Hy- IQ Water ([H9O4] | [H5O2])

Hydrogen Cation .77%

PURPOSE

Antimicrobial

INDICATIONS AND USAGE

For spraying on hands or hard surfaces in order to prevent the spreading of bacteria & harmful germs.

WARNINGS

For External use only. Do not use if you are allergic to any ingredients. Stop use if a rash develops and ask a doctor right away.

Keep out of reach of children

DOSAGE AND ADMINISTRATION

Spray liberally on hard surfaces or hands. Allow to either dry naturally by air, or by drying with a clean paper towel, fabric towel or sponge

OTHER SAFETY INFORMATION

Store under 110°F (43C)

INACTIVE INGREDIENT

Water, UREA

Hy-IQ HAND and SURFACE DISINFECTANT AND SANITIZER